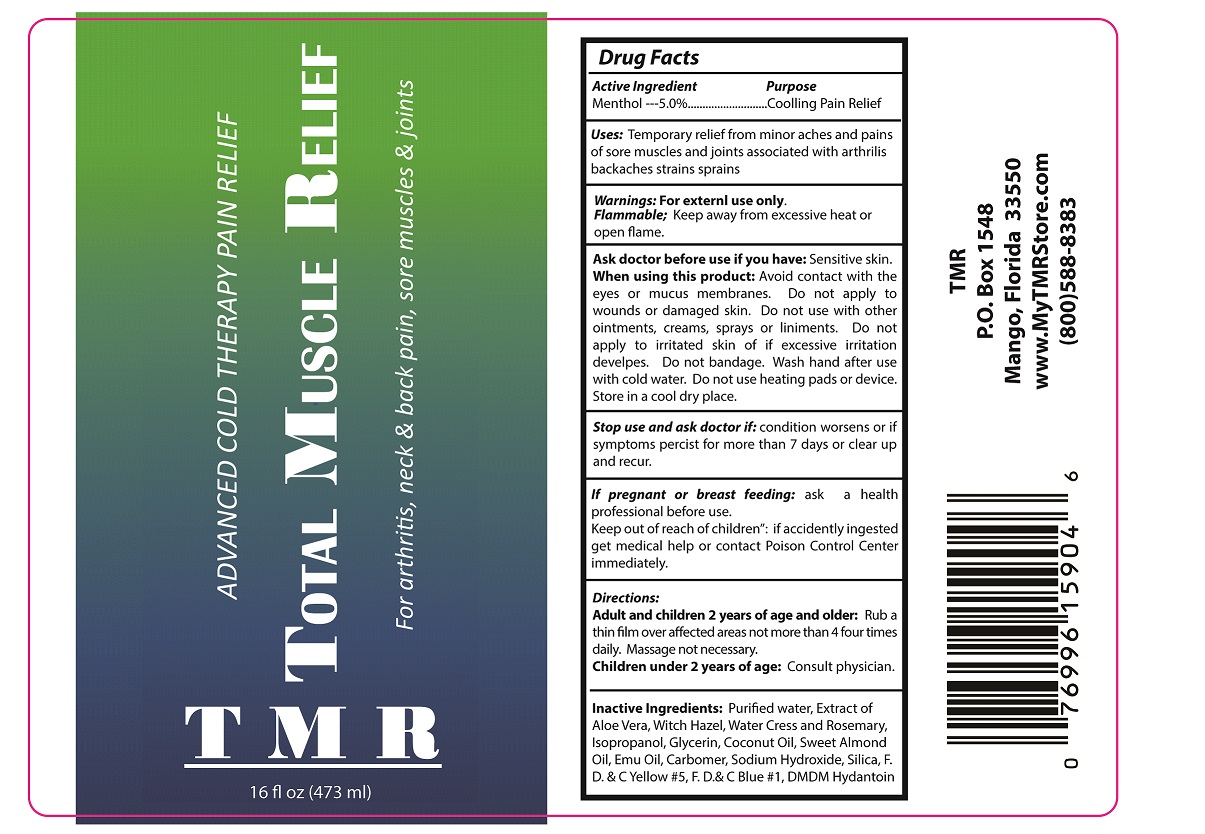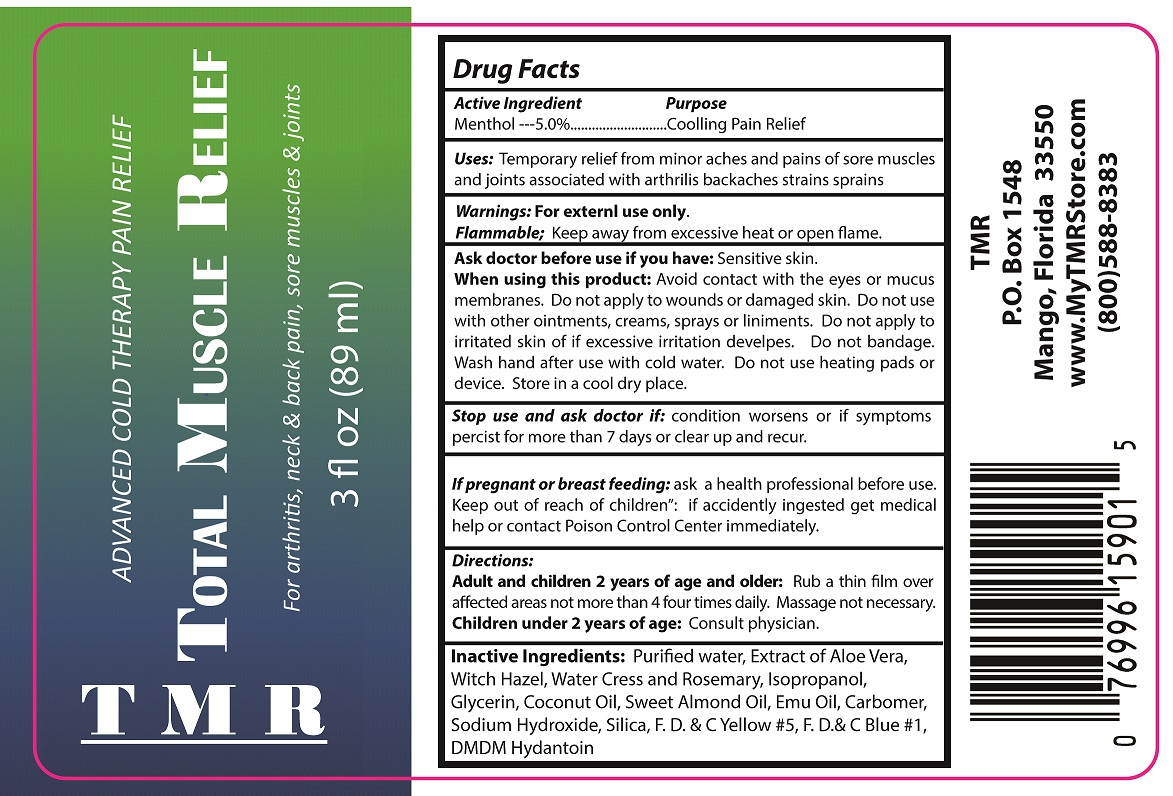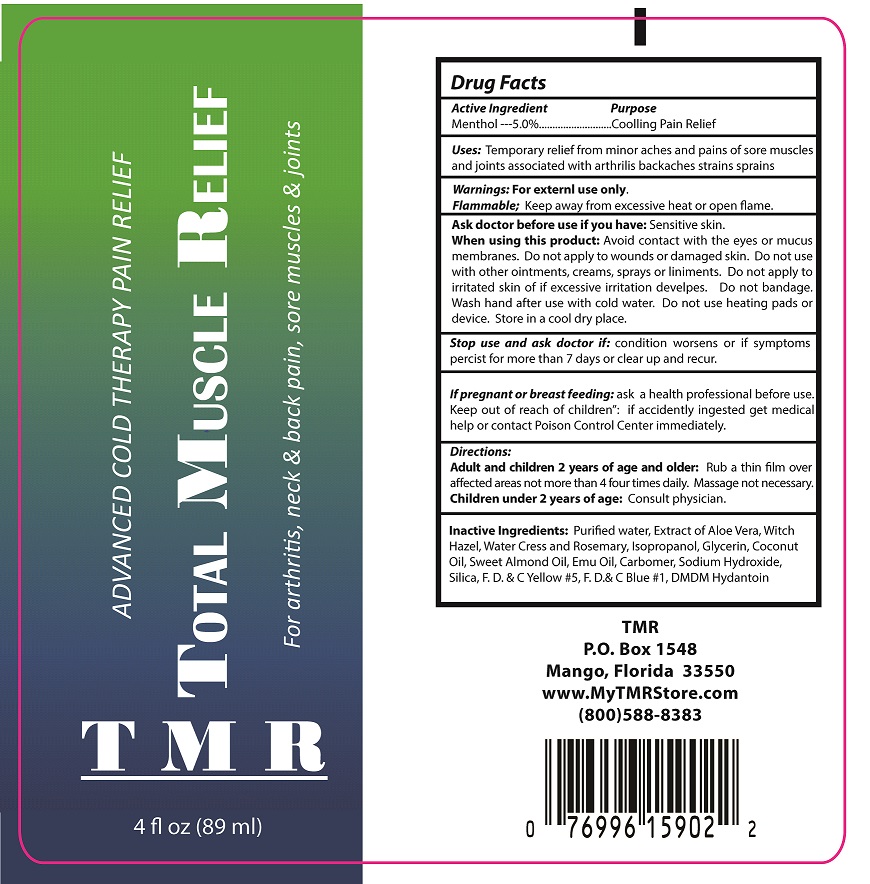 DRUG LABEL: TOTAL MUSCLE RELIEF
NDC: 50130-108 | Form: GEL
Manufacturer: Electrostim Medical Services Inc. d/b/a EMSI
Category: otc | Type: HUMAN OTC DRUG LABEL
Date: 20190227

ACTIVE INGREDIENTS: MENTHOL 5.0 g/100 mL
INACTIVE INGREDIENTS: WATER; ALOE VERA LEAF; WITCH HAZEL; WATERCRESS; ROSEMARY; ISOPROPYL ALCOHOL; GLYCERIN; COCONUT OIL; ALMOND OIL; EMU OIL; CARBOMER HOMOPOLYMER TYPE C (ALLYL PENTAERYTHRITOL CROSSLINKED); SODIUM HYDROXIDE; SILICON DIOXIDE; FD&C YELLOW NO. 5; FD&C BLUE NO. 1; DMDM HYDANTOIN

ACTIVE INGREDIENT

Menthol ---5.0%

PURPOSE

Cooling Pain Relief

USES

Temporary relief from minor aches and pains of sore muscles and joints associated with arthrilis backaches strains sprains

WARNINGS

FOR EXTERNAL USE ONLY.

FLAMMABLE; KEEP AWAY FROM EXCESSIVE HEAT OR OPEN FLAME.

Ask doctor before use if you have: Sensitive skin. When using this product: Avoid contact with the eyes or mucus membranes. Do not apply to wounds or damaged skin. Do not use with other ointments, creams, sprays or liniments. Do not apply to irritated skin of if excessive irritation develpes. Do not bandage. Wash hand after use with cold water. Do not use heating pads or device. Store in a cool dry place.

Stop use and ask doctor if: condition worsens or if symptoms percist for more than 7 days or clear up and recur.

If pregnant or breast feeding: ask a health professional before use.

Keep out of reach of children: if accidently ingested get medical help or contact Poison Control Center immediately.

DIRECTIONS

ADULT AND CHILDREN 2 YEARS OF AGE AND OLDER: RUB A THIN FILM OVER AFFECTED AREAS NOT MORE THAN 4 TIMES DAILY. MASSAGE NOT NECESSARY.

CHILDREN UNDER 2 YEARS OF AGE: CONSULT PHYSICIAN.

INACTIVE INGREDIENTS

PURIFIED WATER, Extract of Aloe Vera, Witch Hazel, Water Cress and Rosemary, Isopropanol, Glycerin, Coconut Oil, Sweet Almond Oil, Emu Oil, Carbomer, Sodium Hydroxide, Silica, F. D. & C Yellow #5, F. D.& C Blue #1, DMDM Hydantoin